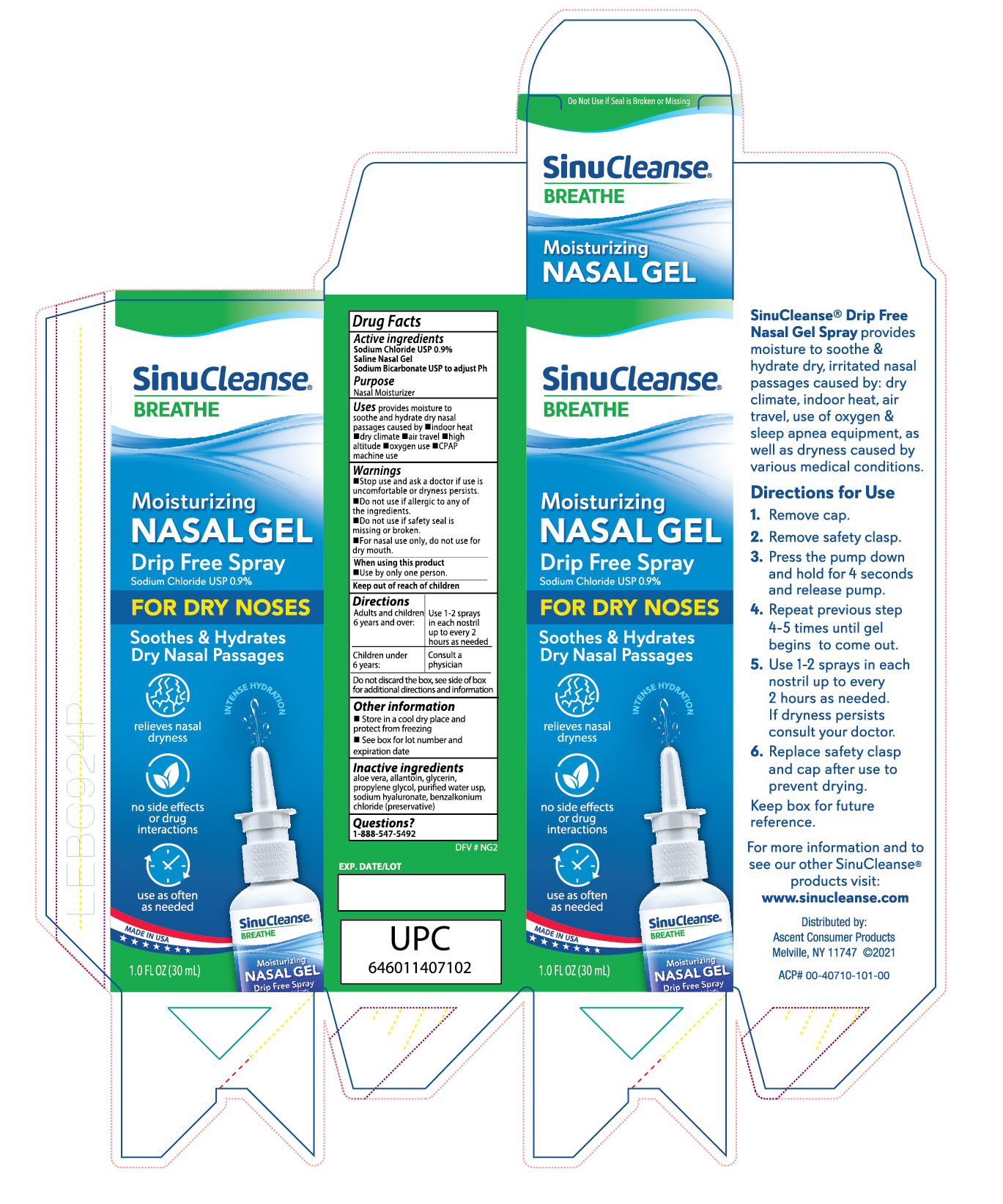 DRUG LABEL: SinuCleanse Nasal Drip
NDC: 42829-407 | Form: GEL
Manufacturer: ASCENT CONSUMER PRODUCTS, INC
Category: otc | Type: HUMAN OTC DRUG LABEL
Date: 20220108

ACTIVE INGREDIENTS: SODIUM CHLORIDE 0.9 mg/100 mL
INACTIVE INGREDIENTS: WATER; ALLANTOIN; GLYCERIN; BENZALKONIUM CHLORIDE; ALOE VERA LEAF; PROPYLENE GLYCOL; HYALURONATE SODIUM

SinuCleanse Breathe Moisturizing Nasal Gel - Drip Free Spray

Active Ingredient

Sodium Chloride 0.9%

Saline Nasal Gel,

Sodium Bicarbonate to adjust pH

Purpose

Nasal Moisturizer

Uses

- Provides moisture to soothe and hydrate dry nasal passages caused by Indoor heat, dry climate, air travel, high altitude, oxygen use, CPAP machineuse

Directions

Adults and children 4 years and over: Use as often as needed
Children under 4 years: Consult a physician
See directions on can for complere instructions

For nasal use only.

Before use, expel a shoet stream of mist into the air. Insert tip of nozzle into one nostril and press down on the textured area at the base of the nozzle so that a gentle mist coats nasal passages. Blow your nose very gently to clear the mucus out. Repeat for the other nostriil.

To flush and irrigate, tilt head to the side over sink. Insert top of nozzle into the top nostril, pressing down on the textured area at the base of the nozzle so that a gentle mist fills sinus passages and flows out the opposite nostril. Repeat in other nostril.

Wipe nozzle after each use.

Warnings

-Stop use and ask a doctor if use is uncomfortable or dryness persists

-Do not use if allergic to any of the ingredients

-Do not use if the safety seal is missing or broken

- For nasal use only, do not use for dry mouth

Other Information

-Store in cool dry place and protect freezing

-See box for lot number and expiration date

Inactive ingredients

aloe vera, allantoin, glycerin, propylene glycol, purified water USP, sodium hyaluronate, benzalkonium chloride

QUESTIONS ?

1-888-547-5492